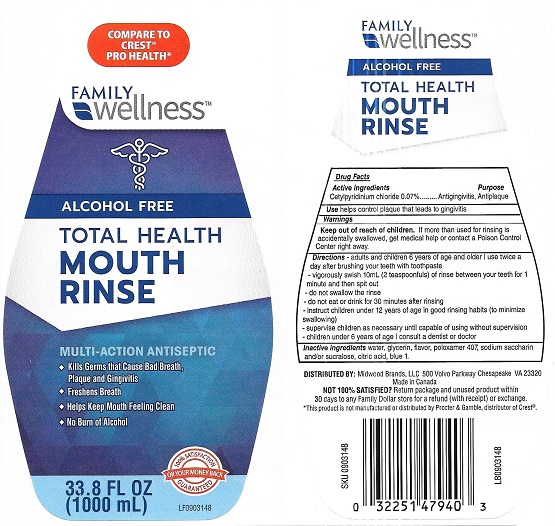 DRUG LABEL: Family Wellness
NDC: 55319-234 | Form: RINSE
Manufacturer: Family Dollar Services Inc.
Category: otc | Type: HUMAN OTC DRUG LABEL
Date: 20210823

ACTIVE INGREDIENTS: CETYLPYRIDINIUM CHLORIDE 0.07 g/100 mL
INACTIVE INGREDIENTS: GLYCERIN; WATER; POLOXAMER 407; SUCRALOSE; SACCHARIN SODIUM; CITRIC ACID MONOHYDRATE; FD&C BLUE NO. 1

Family Wellness Total Health Mouth Rinse Alcohol Free

Drug Facts

Active ingredients
Cetylpyridinium chloride 0.07%

Purpose

Antigingivitis, Antiplaque

INDICATIONS AND USAGE

Usehelps control plaque that leads to gingivitis

Warnings

Keep out of reach of children. If more than used for rinsing is accidentally swallowed, get medical help or contact a Poison Control Center right away.

Directions

- adults and children 6 years of age and older: use twice a day after brushing your teeth with toothpaste
- vigorously swish 10 mL (2 teaspoonfuls) of rinse between your teeth for 1 minute and then spit out
- do not swallow the rinse
- do not eat or drink for 30 minutes after rinsing
- instruct children under 12 years of age in good rinsing habits (to minimize swallowing)
- supervise children as necessary until capable of using without supervision
- children under 6 years of age: consult a dentist or doctor

INACTIVE INGREDIENT

Inactive ingredients water, glycerin, flavor, poloxamer 407, sodium saccharin and/or sucralose, citric acid, blue 1.

DISTRIBUTED BY: Midwood Brands, LLC 500 Volvo Parkway, Chesapeake, VA 23320

Made in Canada

* This product is not manufactured or distributed by Proctor and Gamble, distributor of Crest®.

PACKAGE LABEL

COMPARE TO CREST® PRO HEALTH*

FAMILY wellness™

ALCOHOL FREE

TOTAL HEALTH

MOUTH RINSE

MULTI-ACTION ANTISEPTIC

- Kills Germs that Cause Bad Breath, Plaque and Gingivitis
- Freshens Breath
- Helps Keep Mouth Feeling Clean
- No Burn of Alcohol

33.8 FL OZ (1000 mL)